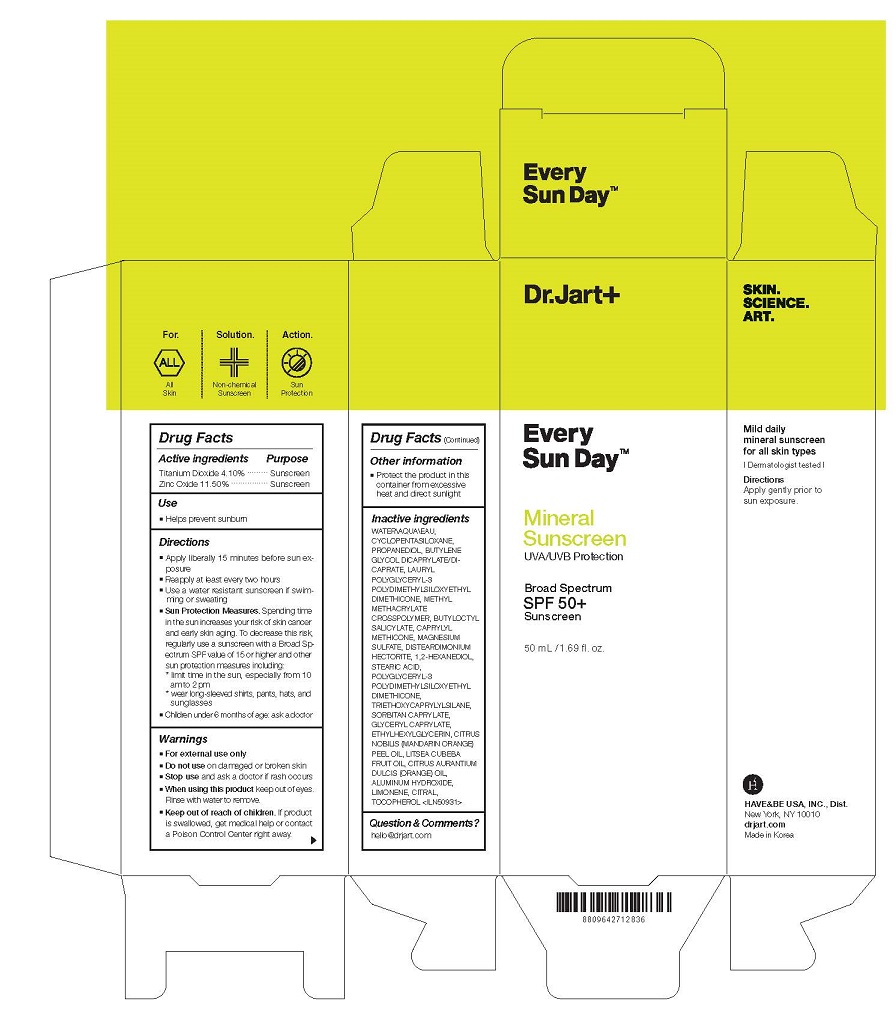 DRUG LABEL: DR.JART EVERY SUN DAY MINERAL SUN SCREEN
NDC: 49404-153 | Form: CREAM
Manufacturer: Have & Be Co., Ltd.
Category: otc | Type: HUMAN OTC DRUG LABEL
Date: 20241225

ACTIVE INGREDIENTS: ZINC OXIDE 115 mg/1 mL; TITANIUM DIOXIDE 41 mg/1 mL
INACTIVE INGREDIENTS: CYCLOMETHICONE 5; METHYL METHACRYLATE/GLYCOL DIMETHACRYLATE CROSSPOLYMER; CITRAL; TOCOPHEROL; ORANGE OIL; ALUMINUM HYDROXIDE; LIMONENE, (+)-; 1,2-HEXANEDIOL; SORBITAN MONOCAPRYLATE; MANDARIN OIL; LITSEA OIL; DISTEARDIMONIUM HECTORITE; PROPANEDIOL; POLYGLYCERYL-3 POLYDIMETHYLSILOXYETHYL DIMETHICONE (4000 MPA.S); GLYCERYL CAPRYLATE; ETHYLHEXYLGLYCERIN; CAPRYLYL TRISILOXANE; BUTYLOCTYL SALICYLATE; WATER; BUTYLENE GLYCOL DICAPRYLATE/DICAPRATE; MAGNESIUM SULFATE, UNSPECIFIED; STEARIC ACID; TRIETHOXYCAPRYLYLSILANE

[NEW] Dr.Jart Every Sun Day Mineral Sun Screen

Active ingredients

Titanium Dioxide 4.10%

Zinc Oxide 11.50%

Purpose

Sunscreen

Use

■ Helps prevent sunburn

Warnings

For external use only

Do not use

on damaged or broken skin

Stop use

and ask a doctor if rash occurs

When using this product

keep out of eyes.
Rinse with water to remove.

Keep out of reach of children.

If product
is swallowed, get medical help or contact
a Poison Control Center right away.

Directions

Apply liberally 15 minutes before sun exposure
■ Reapply at least every two hours
■ Use a water resistant sunscreen if swimming
or sweating
■ Sun Protection Measures. Spending time
in the sun increases your risk of skin cancer
and early skin aging. To decrease this risk,
regularly use a sunscreen with a Broad Spectrum
SPF value of 15 or higher and other
sun protection measures including:
* limit time in the sun, especially from 10
am to 2 pm
* wear long-sleeved shirts, pants, hats, and
sunglasses
■ Children under 6 months of age: ask a doctor

Inactive ingredients

WATER\AQUA\EAU,
CYCLOPENTASILOXANE,
PROPANEDIOL, BUTYLENE
GLYCOL DICAPRYLATE/DICAPRATE,
LAURYL
POLYGLYCERYL-3
POLYDIMETHYLSILOXYETHYL
DIMETHICONE, METHYL
METHACRYLATE
CROSSPOLYMER, BUTYLOCTYL
SALICYLATE, CAPRYLYL
METHICONE, MAGNESIUM
SULFATE, DISTEARDIMONIUM
HECTORITE, 1,2-HEXANEDIOL,
STEARIC ACID,
POLYGLYCERYL-3
POLYDIMETHYLSILOXYETHYL
DIMETHICONE,
TRIETHOXYCAPRYLYLSILANE,
SORBITAN CAPRYLATE,
GLYCERYL CAPRYLATE,
ETHYLHEXYLGLYCERIN, CITRUS
NOBILIS (MANDARIN ORANGE)
PEEL OIL, LITSEA CUBEBA
FRUIT OIL, CITRUS AURANTIUM
DULCIS (ORANGE) OIL,
ALUMINUM HYDROXIDE,
LIMONENE, CITRAL,
TOCOPHEROL <ILN50931>

Other information

■ Protect the product in this
container from excessive
heat and direct sunlight

Principal Display Panel

Dr,Jart+

Every Sun Day
Mineral Sunscreen"/uva/UVB Protection

Broad Spectrum SPF50+ Sunscreen
50ml/1.69fl. oz.